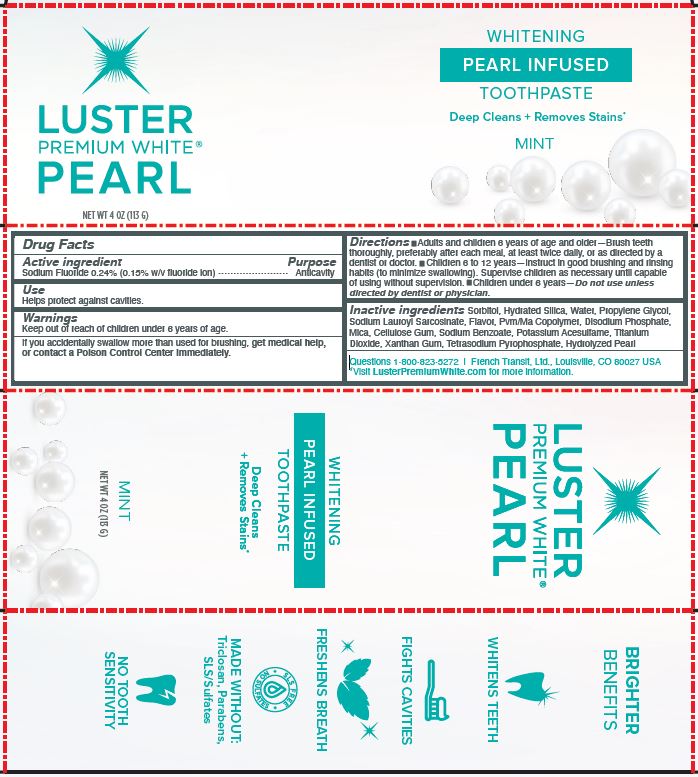 DRUG LABEL: LUSTER PREMIUM WHITE
NDC: 72805-102 | Form: GEL, DENTIFRICE
Manufacturer: French Transit, Ltd
Category: otc | Type: HUMAN OTC DRUG LABEL
Date: 20201024

ACTIVE INGREDIENTS: SODIUM FLUORIDE .24 g/100 g
INACTIVE INGREDIENTS: SORBITOL; HYDRATED SILICA; WATER; PROPYLENE GLYCOL; SODIUM LAUROYL SARCOSINATE; COPOVIDONE K25-31; SODIUM PHOSPHATE, DIBASIC, ANHYDROUS; MICA; CARBOXYMETHYLCELLULOSE SODIUM, UNSPECIFIED; SODIUM BENZOATE; POTASSIUM ACETATE; TITANIUM DIOXIDE; XANTHAN GUM; SODIUM PYROPHOSPHATE; CALCIUM CARBONATE

LUSTER PREMIUM WHITE PEARL

ACTIVE INGREDIENT

SODIUM FLUORIDE 0.24% (0.15% W/V FLUORIDE ION)

PURPOSE

ANTICAVITY

USE

HELPS PROTECT AGAINST CAVITIES.

WARNINGS

If you accidentally swallow more than used for brushing, get medical help,

Keep out of reach of children under 6 years of age.

DIRECTIONS

- Adults and children 6 years of age and older—Brush teeth thoroughly, preferably after each meal, at least twice daily, or as directed by adentist or doctor.
- Children 6 to 12 years—Instruct in good brushing and rinsing habits (to minimize swallowing). Supervise children as necessary until capable of using without supervision.
- Children under 6 years—Do not use unless directed by dentist or physician.

INACTIVE INGREDIENTS

Sorbitol, Hydrated Silica, Water, Propylene Glycol, Sodium Lauroyl Sarcosinate, Flavor, Pvm/Ma Copolymer, Disodium Phosphate, Mica, Cellulose Gum, Sodium Benzoate, Potassium Acesulfame, Titanium Dioxide, Xanthan Gum, Tetrasodium Pyrophosphate, Hydrolyzed Pearl

QUESTIONS

1-800-823-5272 | French Transit, Ltd., Louisville, CO 80027 USA
*Visit LusterPremiumWhite.com for more information.